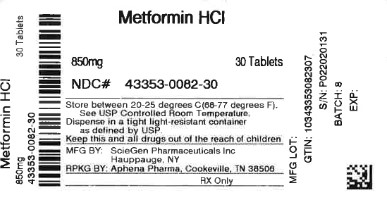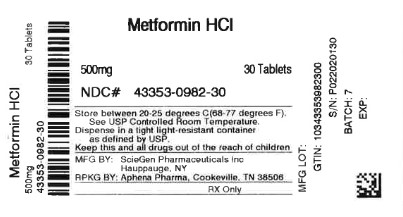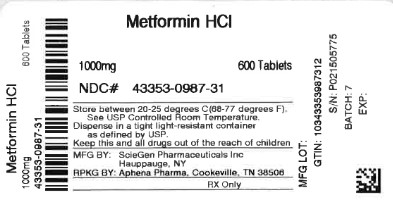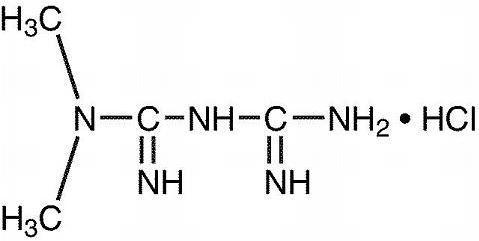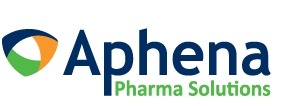 DRUG LABEL: METFORMIN HYDROCHLORIDE
NDC: 43353-982 | Form: TABLET
Manufacturer: Aphena Pharma Solutions - Tennessee, LLC
Category: prescription | Type: HUMAN PRESCRIPTION DRUG LABEL
Date: 20260122

ACTIVE INGREDIENTS: METFORMIN HYDROCHLORIDE 500 mg/1 1
INACTIVE INGREDIENTS: STARCH, CORN; POVIDONE, UNSPECIFIED; CROSPOVIDONE (120 .MU.M); MAGNESIUM STEARATE; HYPROMELLOSE 2910 (6 MPA.S); POLYETHYLENE GLYCOL 400; POLYETHYLENE GLYCOL 8000

Metformin Hydrochloride Tablets, USP

Lactic Acidosis

Lactic acidosis is a rare, but serious, metabolic complication that can occur due to metformin accumulation during treatment with metformin hydrochloride tablets; when it occurs, it is fatal in approximately 50% of cases. Lactic acidosis may also occur in association with a number of pathophysiologic conditions, including diabetes mellitus, and whenever there is significant tissue hypoperfusion and hypoxemia. Lactic acidosis is characterized by elevated blood lactate levels (>5 mmol/L), decreased blood pH, electrolyte disturbances with an increased anion gap, and an increased lactate/pyruvate ratio. When metformin is implicated as the cause of lactic acidosis, metformin plasma levels >5 mcg/mL are generally found.

The reported incidence of lactic acidosis in patients receiving metformin hydrochloride is very low (approximately 0.03 cases/1000 patient-years, with approximately 0.015 fatal cases/1000 patient-years). In more than 20,000 patient-years exposure to metformin in clinical trials, there were no reports of lactic acidosis. Reported cases have occurred primarily in diabetic patients with significant renal insufficiency, including both intrinsic renal disease and renal hypoperfusion, often in the setting of multiple concomitant medical/surgical problems and multiple concomitant medications. Patients with congestive heart failure requiring pharmacologic management, in particular those with unstable or acute congestive heart failure who are at risk of hypoperfusion and hypoxemia, are at increased risk of lactic acidosis. The risk of lactic acidosis increases with the degree of renal dysfunction and the patient's age. The risk of lactic acidosis may, therefore, be significantly decreased by regular monitoring of renal function in patients taking metformin hydrochloride tablets and by use of the minimum effective dose of metformin hydrochloride tablets. In particular, treatment of the elderly should be accompanied by careful monitoring of renal function. Metformin hydrochloride tablet treatment should not be initiated in patients>80 years of age unless measurement of creatinine clearance demonstrates that renal function is not reduced, as these patients are more susceptible to developing lactic acidosis. In addition, metformin hydrochloride tablets should be promptly withheld in the presence of any condition associated with hypoxemia, dehydration, or sepsis. Because impaired hepatic function may significantly limit the ability to clear lactate, metformin hydrochloride tablets should generally be avoided in patients with clinical or laboratory evidence of hepatic disease. Patients should be cautioned against excessive alcohol intake, either acute or chronic, when taking metformin hydrochloride tablets, since alcohol potentiates the effects of metformin hydrochloride on lactate metabolism. In addition, metformin hydrochloride tablets should be temporarily discontinued prior to any intravascular radiocontrast study and for any surgical procedure (see also PRECAUTIONS).

The onset of lactic acidosis often is subtle, and accompanied only by nonspecific symptoms such as malaise, myalgias, respiratory distress, increasing somnolence, and nonspecific abdominal distress. There may be associated hypothermia, hypotension, and resistant bradyarrhythmias with more marked acidosis. The patient and the patient's physician must be aware of the possible importance of such symptoms and the patient should be instructed to notify the physician immediately if they occur (see also PRECAUTIONS). Metformin hydrochloride tablets should be withdrawn until the situation is clarified. Serum electrolytes, ketones, blood glucose, and if indicated, blood pH, lactate levels, and even blood metformin levels may be useful. Once a patient is stabilized on any dose level of Metformin hydrochloride tablets, gastrointestinal symptoms, which are common during initiation of therapy, are unlikely to be drug related. Later occurrence of gastrointestinal symptoms could be due to lactic acidosis or other serious disease.

Levels of fasting venous plasma lactate above the upper limit of normal but less than 5 mmol/L in patients taking metformin hydrochloride tablets do not necessarily indicate impending lactic acidosis and may be explainable by other mechanisms, such as poorly controlled diabetes or obesity, vigorous physical activity, or technical problems in sample handling. (See also PRECAUTIONS.)

Lactic acidosis should be suspected in any diabetic patient with metabolic acidosis lacking evidence of ketoacidosis (ketonuria and ketonemia).

Lactic acidosis is a medical emergency that must be treated in a hospital setting. In a patient with lactic acidosis who is taking metformin hydrochloride tablets, the drug should be discontinued immediately and general supportive measures promptly instituted. Because metformin hydrochloride is dialyzable (with a clearance of up to 170 mL/min under good hemodynamic conditions), prompt hemodialysis is recommended to correct the acidosis and remove the accumulated metformin. Such management often results in prompt reversal of symptoms and recovery. (See also CONTRAINDICATIONSand PRECAUTIONS.)

DESCRIPTION

Metformin Hydrochloride Tablets USP, are oral antihyperglycemic drugs used in the management of type 2 diabetes. Metformin hydrochloride (N,N-dimethylimidodicarbonimidic diamide hydrochloride) is not chemically or pharmacologically related to any other classes of oral antihyperglycemic agents. The structural formula is as shown:

Metformin hydrochloride is a white crystalline compound with a molecular formula of C4H11N5• HCl and a molecular weight of 165.63. Metformin hydrochloride is freely soluble in water, slightly soluble in alcohol, practically insoluble in acetone and in methylene hydrochloride. The pKa of metformin is 12.4. The pH of a 1% aqueous solution of metformin hydrochloride is 6.68.

Each Metformin Hydrochloride Tablets contain 500 mg, 850 mg, or 1000 mg of metformin hydrochloride. Each tablet contains the inactive ingredients pregelatinized starch (maize), povidone, crospovidone, magnesium stearate. In addition, the coating for the tablets contains hypromellose polyethylene glycol, titanium dioxide and flavoring agent contains dextrose, ethyl alcohol, gum arabic, propylene glycol and silicon dioxide.

CLINICAL PHARMACOLOGY

Mechanism of Action

Metformin is an antihyperglycemic agent which improves glucose tolerance in patients with type 2 diabetes, lowering both basal and postprandial plasma glucose. Its pharmacologic mechanisms of action are different from other classes of oral antihyperglycemic agents. Metformin decreases hepatic glucose production, decreases intestinal absorption of glucose, and improves insulin sensitivity by increasing peripheral glucose uptake and utilization. Unlike sulfonylureas, metformin does not produce hypoglycemia in either patients with type 2 diabetes or normal subjects (except in special circumstances, see PRECAUTIONS) and does not cause hyperinsulinemia. With metformin therapy, insulin secretion remains unchanged while fasting insulin levels and day-long plasma insulin response may actually decrease.

Absorption and Bioavailability

The absolute bioavailability of a metformin hydrochloride 500 mg tablet given under fasting conditions is approximately 50 to 60%. Studies using single oral doses of metformin hydrochloride 500 mg to 1500 mg, and 850 mg to 2550 mg, indicate that there is a lack of dose proportionality with increasing doses, which is due to decreased absorption rather than an alteration in elimination. Food decreases the extent of and slightly delays the absorption of metformin, as shown by approximately a 40% lower mean peak plasma concentration (Cmax), a 25% lower area under the plasma concentration versus time curve (AUC), and a 35-minute prolongation of time to peak plasma concentration (Tmax) following administration of a single 850 mg tablet of metformin with food, compared to the same tablet strength administered fasting. The clinical relevance of these decreases is unknown.

Distribution

The apparent volume of distribution (V/F) of metformin following single oral doses of metformin hydrochloride tablets 850 mg averaged 654 ± 358 L. Metformin is negligibly bound to plasma proteins, in contrast to sulfonylureas, which are more than 90% protein bound. Metformin partitions into erythrocytes, most likely as a function of time. At usual clinical doses and dosing schedules of metformin hydrochloride tablets, steady state plasma concentrations of metformin are reached within 24 to 48 hours and are generally <1 mcg/mL. During controlled clinical trials of metformin hydrochloride tablets, maximum metformin plasma levels did not exceed 5 mcg/mL, even at maximum doses.

Metabolism and Elimination

Intravenous single-dose studies in normal subjects demonstrate that metformin is excreted unchanged in the urine and does not undergo hepatic metabolism (no metabolites have been identified in humans) nor biliary excretion. Renal clearance (see Table 1) is approximately 3.5 times greater than creatinine clearance, which indicates that tubular secretion is the major route of metformin elimination. Following oral administration, approximately 90% of the absorbed drug is eliminated via the renal route within the first 24 hours, with a plasma elimination half-life of approximately 6.2 hours. In blood, the elimination half-life is approximately 17.6 hours, suggesting that the erythrocyte mass may be a compartment of distribution.

Special Populations

Patients with Type 2 Diabetes

In the presence of normal renal function, there are no differences between single- or multiple-dose pharmacokinetics of metformin between patients with type 2 diabetes and normal subjects (see Table 1), nor is there any accumulation of metformin in either group at usual clinical doses.

Renal Insufficiency

In patients with decreased renal function (based on measured creatinine clearance), the plasma and blood half-life of metformin is prolonged and the renal clearance is decreased in proportion to the decrease in creatinine clearance (see Table 1;also see WARNINGS).

Hepatic Insufficiency

No pharmacokinetic studies of metformin have been conducted in patients with hepatic insufficiency.

Geriatrics

Limited data from controlled pharmacokinetic studies of metformin hydrochloride tablets in healthy elderly subjects suggest that total plasma clearance of metformin is decreased, the half-life is prolonged, and Cmaxis increased, compared to healthy young subjects. From these data, it appears that the change in metformin pharmacokinetics with aging is primarily accounted for by a change in renal function (see Table 1). Metformin treatment should not be initiated in patients ≥80 years of age unless measurement of creatinine clearance demonstrates that renal function is not reduced (see WARNINGSand DOSAGE AND ADMINISTRATION).

Table 1: Select Mean (±S.D.) Metformin Pharmacokinetic Parameters Following Single or Multiple Oral Doses of Metformin Hydrochloride Tablets
Subject Groups:; Metformin hydrochloride tablets dosea; (number of subjects) | Cmaxb; (mcg/mL) | Tmaxc; (hrs) | Renal Clearance; (mL/min)
Healthy, nondiabetic adults:; 500 mg single dose (24); 850 mg single dose (74)d; 850 mg three times daily for 19 dosese(9) | 1.03 (±0.33); 1.60 (±0.38); 2.01 (±0.42) | 2.75 (±0.81); 2.64 (±0.82); 1.79 (±0.94) | 600 (±132); 552 (±139); 642 (±173)
Adults with type 2 diabetes:; 850 mg single dose (23); 850 mg three times daily for 19 dosese(9) | 1.48 (±0.5); 1.90 (±0.62) | 3.32 (±1.08); 2.01 (±1.22) | 491 (±138); 550 (±160)
Elderlyf, healthy nondiabetic adults:; 850 mg single dose (12) | 2.45 (±0.70) | 2.71 (±1.05) | 412 (±98)
Renal-impaired adults:; 850 mg single dose; Mild(CLcrg61to 90 mL/min) (5); Moderate(CLcr31to 60 mL/ min) (4); Severe(CLcr10 to 30 mL/min)(6) | 1.86 (±0.52); 4.12 (±1.83); 3.93 (±0.92) | 3.20 (±0.45); 3.75 (±0.50); 4.01 (±1.10) | 384 (±122); 108 (±57); 130 (±90)

aAll doses given fasting except the first 18 doses of the multiple dose studies

bPeak plasma concentration

cTime to peak plasma concentration

dCombined results (average means) of five studies: mean age 32 years (range 23 to 59 years)

eKinetic study done following dose 19, given fasting

fElderly subjects, mean age 71 years (range 65 to 81 years)

gCLcr= creatinine clearance normalized to body surface area of 1.73 m^2

Pediatrics

After administration of a single oral metformin 500 mg tablet with food, geometric mean metformin Cmaxand AUC differed less than 5% between pediatric type 2 diabetic patients (12 to 16 years of age) and gender- and weight-matched healthy adults (20 to 45 years of age), all with normal renal function.

Gender

Metformin pharmacokinetic parameters did not differ significantly between normal subjects and patients with type 2 diabetes when analyzed according to gender (males = 19, females= 16). Similarly, in controlled clinical studies in patients with type 2 diabetes, the antihyperglycemic effect of metformin hydrochloride tablet was comparable in males and females.

No studies of metformin pharmacokinetic parameters according to race have been performed. In controlled clinical studies of metformin hydrochloride tablets in patients with type 2 diabetes, the antihyperglycemic effect was comparable in whites (n=249), blacks (n=51), and Hispanics (n=24).

Metformin Hydrochloride Tablets

In a double-blind, placebo-controlled, multicenter US clinical trial involving obese patients with type 2 diabetes whose hyperglycemia was not adequately controlled with dietary management alone (baseline fasting plasma glucose [FPG] of approximately 240 mg/dL), treatment with metformin (up to 2550 mg/day) for 29 weeks resulted in significant mean net reductions in fasting and postprandial plasma glucose (PPG) and hemoglobin A1c(HbA1c) of 59 mg/dL, 83 mg/dL, and 1.8%, respectively, compared to the placebo group (see Table 2).

Table 2: Metformin vs Placebo Summary of Mean Changes from Baseline* in Fasting Plasma Glucose, HbA1c, and Body Weight, at Final Visit (29-week study)
 | Metformin HCl; (n=141) | Placebo; (n=145) | p-Value
FPG (mg/dL)
Baseline | 241.5 | 237.7 | NS**
Change at FINAL VISIT | -53.0 | 6.3 | 0.001
Hemoglobin A1c(%)
Baseline | 8.4 | 8.2 | NS**
Change at FINAL VISIT | -1.4 | 0.4 | 0.001
Body Weight (lbs)
Baseline | 201.0 | 206.0 | NS**
Change at FINAL VISIT | -1.4 | -2.4 | NS**

* All patients on diet therapy at Baseline

** Not statistically significant

A 29-week, double-blind, placebo-controlled study of metformin and glyburide, alone and in combination, was conducted in obese patients with type 2 diabetes who had failed to achieve adequate glycemic control while on maximum doses of glyburide (baseline FPG of approximately 250 mg/dL) (see Table 3). Patients randomized to the combination arm started therapy with metformin hydrochloride tablets 500 mg and glyburide 20 mg. At the end of each week of the first four weeks of the trial, these patients had their dosages of metformin hydrochloride tablets increased by 500 mg if they had failed to reach target fasting plasma glucose. After week four, such dosage adjustments were made monthly, although no patient was allowed to exceed metformin hydrochloride tablets 2500 mg. Patients in the metformin hydrochloride tablets only arm (metformin plus placebo) followed the same titration schedule. At the end of the trial, approximately 70% of the patients in the combination group were taking metformin hydrochloride tablets 2000 mg/glyburide 20 mg or metformin hydrochloride tablets 2500 mg/glyburide 20 mg. Patients randomized to continue on glyburide experienced worsening of glycemic control, with mean increases in FPG, PPG, and HbA1cof 14 mg/dL, 3 mg/dL, and 0.2%, respectively. In contrast, those randomized to metformin (up to 2500 mg/day) experienced a slight improvement, with mean reductions in FPG, PPG, and HbA1cof 1 mg/dL, 6 mg/dL, and 0.4%, respectively. The combination of metformin and glyburide was effective in reducing FPG, PPG, and HbA1clevels by 63 mg/dL, 65 mg/dL, and 1.7%, respectively. Compared to results of glyburide treatment alone, the net differences with combination treatment were -77 mg/dL, -68 mg/dL, and -1.9%, respectively (see Table 3).

Table 3: Combined Metformin/Glyburide (Comb) vs Glyburide (Glyb) or Metformin (Met) Monotherapy: Summary of Mean Changes from Baseline* in Fasting Plasma Glucose, HbA1c, and Body Weight, at Final Visit (29-week study)
 |  |  |  |  | p-value
 | Comb; (n=213) | Glyb; (n=209) | Met; (n=210) | Glyb vs Comb | Met vs Comb | Met vs Glyb
Fasting Plasma Glucose; (mg/dL); Baseline; Change at FINAL VISIT | 250.5; -63.5 | 247.5; 13.7 | 253.9; -0.9 | NS**; 0.001 | NS**; 0.001 | NS**; 0.025
Hemoglobin A1c(%); Baseline; Change at FINAL VISIT | 8.8; -1.7 | 8.5; 0.2 | 8.9; -0.4 | NS**; 0.001 | NS**; 0.001 | 0.007; 0.001
Body Weight; (lbs); Baseline; Change at FINAL VISIT | 202.2; 0.9 | 203.0; -0.7 | 204.0; -8.4 | NS**; 0.011 | NS**; 0.001 | NS**; 0.001

* All patients on glyburide, 20 mg/day, at Baseline

** Not statistically significant

The magnitude of the decline in fasting blood glucose concentration following the institution of metformin hydrochloride tablets therapy was proportional to the level of fasting hyperglycemia. Patients with type 2 diabetes with higher fasting glucose concentrations experienced greater declines in plasma glucose and glycosylated hemoglobin.

In clinical studies, metformin, alone or in combination with a sulfonylurea, lowered mean fasting serum triglycerides, total cholesterol, and LDL cholesterol levels, and had no adverse effects on other lipid levels (see Table 4).

Table 4: Summary of Mean Percent Change From Baseline of Major Serum Lipid Variables at Final Visit (29-week studies)
 | Combined | Metformin | Vs Placebo | Metformin/; Vs | Glyburide; Monotherapy
 | Metformin; (n=141) | Placebo; (n=145) | Metformin; (n=210) | Metformin/; Glyburide; (n=213) | Glyburide; (n=209)
Total Cholesterol; (mg/dL); Baseline; Mean % Change at FINAL VISIT | 211.0; -5% | 212.3; 1% | 213.1; -2% | 215.6; -4% | 219.6; 1%
Total Triglycerides; (mg/dL); Baseline; Mean % Change at FINAL VISIT | 236.1; -16% | 203.5; 1% | 242.5; -3% | 215.0; -8% | 266.1; 4%
LDL-Cholesterol; (mg/dL); Baseline; Mean % Change at FINAL VISIT | 135.4; -8% | 138.5; 1% | 134.3; -4% | 136.0; -6% | 137.5; 3%
HDL-Cholesterol; (mg/dL); Baseline; Mean % Change at FINAL VISIT | 39.0; 2% | 40.5; -1% | 37.2; 5% | 39.0; 3% | 37.0; 1%

In contrast to sulfonylureas, body weight of individuals on metformin tended to remain stable or even decrease somewhat (see Tables 2and 3).

A 24-week, double-blind, placebo-controlled study of metformin plus insulin versus insulin plus placebo was conducted in patients with type 2 diabetes who failed to achieve adequate glycemic control on insulin alone (see Table 5). Patients randomized to receive metformin plus insulin achieved a reduction in HbA1cof 2.10%, compared to a 1.56% reduction in HbA1cachieved by insulin plus placebo. The improvement in glycemic control was achieved at the final study visit with 16% less insulin, 93.0 U/day vs 110.6 U/day, metformin plus insulin versus insulin plus placebo, respectively, p=0.04.

Table 5: Combined Metformin/Insulin vs Placebo/Insulin Summary of Mean Changes from Baseline in HbA1cand Daily Insulin Dose
 | Metformin/; Insulin; (n=26) | Placebo/; Insulin; (n=28) | Treatment; Difference; Mean ± SE
Hemoglobin A1c(%); Baseline; Change at FINAL VISIT | 8.95; -2.10 | 9.32; -1.56 | -0.54±0.43a
Insulin Dose (U/day); Baseline; Change at FINAL VISIT | 93.12; -0.15 | 94.64; 15.93 | -16.08±7.77b

aStatistically significant using analysis of covariance with baseline as covariate (p=0.04)

Not significant using analysis of variance (values shown in table)

bStatistically significant for insulin (p=0.04)

A second double-blind, placebo-controlled study (n=51), with sixteen weeks of randomized treatment, demonstrated that in patients with type 2 diabetes controlled on insulin for eight weeks with an average HbA1cof 7.46 ± 0.97%, the addition of metformin maintained similar glycemic control (HbA1c7.15 ± 0.61 vs 6.97 ± 0.62 for metformin plus insulin and placebo plus insulin, respectively) with 19% less insulin versus baseline (reduction of 23.68 ± 30.22 vs an increase of 0.43 ± 25.20 units for metformin plus insulin and placebo plus insulin, p<0.01). In addition, this study demonstrated that the combination of metformin hydrochloride tablets plus insulin resulted in reduction in body weight of 3.11 ± 4.30 lbs, compared to an increase of 1.30 ± 6.08 lbs for placebo plus insulin, p=0.01.

Pediatric Clinical Studies

In a double-blind, placebo-controlled study in pediatric patients aged 10 to 16 years with type 2 diabetes (mean FPG 182.2 mg/dL), treatment with metformin hydrochloride tablets (up to 2000 mg/day) for up to 16 weeks (mean duration of treatment 11 weeks) resulted in a significant mean net reduction in FPG of 64.3 mg/dL, compared with placebo (see Table 6).

Table 6: Metformin vs Placebo (Pediatricsa) Summary of Mean Changes from Baseline* in Plasma Glucose and Body Weight at Final Visit
 | Metformin | Placebo | p-Value
FPG (mg/dL); Baseline; Change at FINAL VISIT | (n=37); 162.4; -42.9 | (n=36); 192.3; 21.4 | <0.001
Body Weight (lbs); Baseline; Change at FINAL VISIT | (n=39); 205.3; -3.3 | (n=38); 189.0; -2.0 | NS**

aPediatric patients mean age 13.8 years (range 10-16 years)

* All patients on diet therapy at Baseline

** Not statistically significant

INDICATIONS AND USAGE

Metformin hydrochloride tablet are indicated as an adjunct to diet and exercise to improve glycemic control in adults and children with type 2 diabetes mellitus.

CONTRAINDICATIONS

Metformin hydrochloride tablets are contraindicated in patients with:

1. Renal disease or renal dysfunction (e.g., as suggested by serum creatinine levels ≥1.5 mg/dL [males], ≥1.4 mg/dL [females] or abnormal creatinine clearance) which may also result from conditions such as cardiovascular collapse (shock), acute myocardial infarction, and septicemia (see WARNINGSand PRECAUTIONS).
2. Known hypersensitivity to metformin hydrochloride.
3. Acute or chronic metabolic acidosis, including diabetic ketoacidosis, with or without coma. Diabetic ketoacidosis should be treated with insulin.

Metformin hydrochloride tablets should be temporarily discontinued in patients undergoing radiologic studies involving intravascular administration of iodinated contrast materials, because use of such products may result in acute alteration of renal function (see also PRECAUTIONS).

WARNINGS

BOXED WARNING

Lactic Acidosis:

Lactic acidosis is a rare, but serious, metabolic complication that can occur due to metformin accumulation during treatment with metformin hydrochloride tablets; when it occurs, it is fatal in approximately 50% of cases. Lactic acidosis may also occur in association with a number of pathophysiologic conditions, including diabetes mellitus, and whenever there is significant tissue hypoperfusion and hypoxemia. Lactic acidosis is characterized by elevated blood lactate levels (>5 mmol/L), decreased blood pH, electrolyte disturbances with an increased anion gap, and an increased lactate/pyruvate ratio. When metformin is implicated as the cause of lactic acidosis, metformin plasma levels >5 µg/mL are generally found.

The reported incidence of lactic acidosis in patients receiving metformin hydrochloride is very low (approximately 0.03 cases/1000 patient-years, with approximately 0.015 fatal cases/ 1000 patient-years). In more than 20,000 patient-years exposure to metformin in clinical trials, there were no reports of lactic acidosis. Reported cases have occurred primarily in diabetic patients with significant renal insufficiency, including both intrinsic renal disease and renal hypoperfusion, often in the setting of multiple concomitant medical/surgical problems and multiple concomitant medications. Patients with congestive heart failure requiring pharmacologic management, in particular those with unstable or acute congestive heart failure who are at risk of hypoperfusion and hypoxemia, are at increased risk of lactic acidosis. The risk of lactic acidosis increases with the degree of renal dysfunction and the patient’s age. The risk of lactic acidosis may, therefore, be significantly decreased by regular monitoring of renal function in patients taking metformin hydrochloride tablets and by use of the minimum effective dose of metformin hydrochloride tablets. In particular, treatment of the elderly should be accompanied by careful monitoring of renal function. Metformin hydrochloride tablets treatment should not be initiated in patients ≥80 years of age unless measurement of creatinine clearance demonstrates that renal function is not reduced, as these patients are more susceptible to developing lactic acidosis. In addition, metformin hydrochloride tablets should be promptly withheld in the presence of any condition associated with hypoxemia, dehydration, or sepsis. Because impaired hepatic function may significantly limit the ability to clear lactate, metformin hydrochloride tablets should generally be avoided in patients with clinical or laboratory evidence of hepatic disease. Patients should be cautioned against excessive alcohol intake, either acute or chronic, when taking metformin hydrochloride tablets, since alcohol potentiates the effects of metformin hydrochloride on lactate metabolism. In addition, metformin hydrochloride tablets should be temporarily discontinued prior to any intravascular radiocontrast study and for any surgical procedure (see also PRECAUTIONS).

The onset of lactic acidosis often is subtle, and accompanied only by nonspecific symptoms such as malaise, myalgias, respiratory distress, increasing somnolence, and nonspecific abdominal distress. There may be associated hypothermia, hypotension, and resistant bradyarrhythmias with more marked acidosis. The patient and the patient’s physician must be aware of the possible importance of such symptoms and the patient should be instructed to notify the physician immediately if they occur (see also PRECAUTIONS). Metformin hydrochloride tablets should be withdrawn until the situation is clarified. Serum electrolytes, ketones, blood glucose, and if indicated, blood pH, lactate levels, and even blood metformin levels may be useful. Once a patient is stabilized on any dose level of metformin hydrochloride tablets, gastrointestinal symptoms, which are common during initiation of therapy, are unlikely to be drug related. Later occurrence of gastrointestinal symptoms could be due to lactic acidosis or other serious disease.

Levels of fasting venous plasma lactate above the upper limit of normal but less than 5 mmol/L in patients taking metformin hydrochloride tablets do not necessarily indicate impending lactic acidosis and may be explainable by other mechanisms, such as poorly controlled diabetes or obesity, vigorous physical activity, or technical problems in sample handling (see also PRECAUTIONS).

Lactic acidosis should be suspected in any diabetic patient with metabolic acidosis lacking evidence of ketoacidosis (ketonuria and ketonemia).

Lactic acidosis is a medical emergency that must be treated in a hospital setting. In a patient with lactic acidosis who is taking metformin hydrochloride tablets, the drug should be discontinued immediately and general supportive measures promptly instituted. Because metformin hydrochloride is dialyzable (with a clearance of up to 170 mL/min under good hemodynamic conditions), prompt hemodialysis is recommended to correct the acidosis and remove the accumulated metformin. Such management often results in prompt reversal of symptoms and recovery (see also CONTRAINDICATIONSand PRECAUTIONS).

PRECAUTIONS

General

Macrovascular Outcomes—There have been no clinical studies establishing conclusive evidence of macrovascular risk reduction with metfomin hydrochloride tablets or any other anti-diabetic drug.

Monitoring of renal function—Metformin is known to be substantially excreted by the kidney, and the risk of metformin accumulation and lactic acidosis increases with the degree of impairment of renal function. Thus, patients with serum creatinine levels above the upper limit of normal for their age should not receive metformin hydrochloride tablets. In patients with advanced age, metformin should be carefully titrated to establish the minimum dose for adequate glycemic effect, because aging is associated with reduced renal function. In elderly patients, particularly those ≥80 years of age, renal function should be monitored regularly and, generally, metformin hydrochloride tablets should not be titrated to the maximum dose (see WARNINGSand DOSAGE AND ADMINISTRATION).

Before initiation of metformin therapy and at least annually thereafter, renal function should be assessed and verified as normal. In patients in whom development of renal dysfunction is anticipated, renal function should be assessed more frequently and metformin discontinued if evidence of renal impairment is present.

Use of concomitant medications that may affect renal function or metformin disposition—Concomitant medication(s) that may affect renal function or result in significant hemodynamic change or may interfere with the disposition of metformin, such as cationic drugs that are eliminated by renal tubular secretion (see PRECAUTIONS: Drug Interactions), should be used with caution.

Radiologic studies involving the use of intravascular iodinated contrast materials (for example, intravenous urogram, intravenous cholangiography, angiography, and computed tomography (CT) scans with intravascular contrast materials)—Intravascular contrast studies with iodinated materials can lead to acute alteration of renal function and have been associated with lactic acidosis in patients receiving metformin (see CONTRAINDICATIONS). Therefore, in patients in whom any such study is planned, metformin should be temporarily discontinued at the time of or prior to the procedure, and withheld for 48 hours subsequent to the procedure and reinstituted only after renal function has been re-evaluated and found to be normal.

Hypoxic states—Cardiovascular collapse (shock) from whatever cause, acute congestive heart failure, acute myocardial infarction and other conditions characterized by hypoxemia have been associated with lactic acidosis and may also cause prerenal azotemia. When such events occur in patients on metformin therapy, the drug should be promptly discontinued.

Surgical procedures—Metformin therapy should be temporarily suspended for any surgical procedure (except minor procedures not associated with restricted intake of food and fluids) and should not be restarted until the patient’s oral intake has resumed and renal function has been evaluated as normal.

Alcohol intake—Alcohol is known to potentiate the effect of metformin on lactate metabolism. Patients, therefore, should be warned against excessive alcohol intake, acute or chronic, while receiving metformin.

Impaired hepatic function—Since impaired hepatic function has been associated with some cases of lactic acidosis, metformin should generally be avoided in patients with clinical or laboratory evidence of hepatic disease.

Vitamin Bl2levels —In controlled clinical trials of metformin hydrochloride tablets of 29 weeks duration, a decrease to subnormal levels of previously normal serum Vitamin B12levels, without clinical manifestations, was observed in approximately 7% of patients. Such decrease, possibly due to interference with B12absorption from the B12-intrinsic factor complex, is, however, very rarely associated with anemia and appears to be rapidly reversible with discontinuation of metformin hydrochloride tablets or Vitamin B12supplementation. Measurement of hematologic parameters on an annual basis is advised in patients on metformin and any apparent abnormalities should be appropriately investigated and managed (see PRECAUTIONS: Laboratory Tests).

Certain individuals (those with inadequate Vitamin B12or calcium intake or absorption) appear to be predisposed to developing subnormal Vitamin B12levels. In these patients, routine serum Vitamin B12measurements at two- to three-year intervals may be useful.

Change in clinical status of patients with previously controlled type 2 diabetes—A patient with type 2 diabetes previously well controlled on metformin who develops laboratory abnormalities or clinical illness (especially vague and poorly defined illness) should be evaluated promptly for evidence of ketoacidosis or lactic acidosis. Evaluation should include serum electrolytes and ketones, blood glucose and, if indicated, blood pH, lactate, pyruvate, and metformin levels. If acidosis of either form occurs, metformin must be stopped immediately and other appropriate corrective measures initiated (see also WARNINGS).

Hypoglycemia—Hypoglycemia does not occur in patients receiving metformin alone under usual circumstances of use, but could occur when caloric intake is deficient, when strenuous exercise is not compensated by caloric supplementation, or during concomitant use with other glucose-lowering agents (such as sulfonylureas and insulin) or ethanol.

Elderly, debilitated, or malnourished patients, and those with adrenal or pituitary insufficiency or alcohol intoxication are particularly susceptible to hypoglycemic effects. Hypoglycemia may be difficult to recognize in the elderly, and in people who are taking beta adrenergic blocking drugs.

Loss of control of blood glucose—When a patient stabilized on any diabetic regimen is exposed to stress such as fever, trauma, infection, or surgery, a temporary loss of glycemic control may occur. At such times, it may be necessary to withhold metformin and temporarily administer insulin. Metformin may be reinstituted after the acute episode is resolved.

The effectiveness of oral antidiabetic drugs in lowering blood glucose to a targeted level decreases in many patients over a period of time. This phenomenon, which may be due to progression of the underlying disease or to diminished responsiveness to the drug, is known as secondary failure, to distinguish it from primary failure in which the drug is ineffective during initial therapy. Should secondary failure occur with either metformin or sulfonylurea monotherapy, combined therapy with metformin and sulfonylurea may result in a response. Should secondary failure occur with combined metformin/sulfonylurea therapy it may be necessary to consider therapeutic alternatives including initiation of insulin therapy.

Information for Patients

Patients should be informed of the potential risks and benefits of metformin and of alternative modes of therapy. They should also be informed about the importance of adherence to dietary instructions, of a regular exercise program, and of regular testing of blood glucose, glycosylated hemoglobin, renal function, and hematologic parameters.

The risks of lactic acidosis, its symptoms, and conditions that predispose to its development, as noted in the WARNINGSand PRECAUTIONS sections, should be explained to patients. Patients should be advised to discontinue metformin immediately and to promptly notify their health practitioner if unexplained hyperventilation, myalgia, malaise, unusual somnolence, or other nonspecific symptoms occur. Once a patient is stabilized on any dose level of metformin, gastrointestinal symptoms, which are common during initiation of metformin therapy, are unlikely to be drug related. Later occurrence of gastrointestinal symptoms could be due to lactic acidosis or other serious disease.

Patients should be counseled against excessive alcohol intake, either acute or chronic, while receiving metformin.

Metformin alone does not usually cause hypoglycemia, although it may occur when metformin is used in conjunction with oral sulfonylureas and insulin. When initiating combination therapy, the risks of hypoglycemia, its symptoms and treatment, and conditions that predispose to its development should be explained to patients and responsible family members (see Patient Informationprinted below).

Laboratory Tests

Response to all diabetic therapies should be monitored by periodic measurements of fasting blood glucose and glycosylated hemoglobin levels, with a goal of decreasing these levels toward the normal range. During initial dose titration, fasting glucose can be used to determine the therapeutic response. Thereafter, both glucose and glycosylated hemoglobin should be monitored. Measurements of glycosylated hemoglobin may be especially useful for evaluating long-term control (see also DOSAGE AND ADMINISTRATION).

Initial and periodic monitoring of hematologic parameters (e.g., hemoglobin/ hematocrit and red blood cell indices) and renal function (serum creatinine) should be performed, at least on an annual basis. While megaloblastic anemia has rarely been seen with metformin hydrochloride tablets therapy, if this is suspected, Vitamin B12deficiency should be excluded.

Drug Interactions (Clinical Evaluation of Drug Interactions Conducted with metformin hydrochloride tablets)

Glyburide—In a single-dose interaction study in type 2 diabetes patients, co-administration of metformin and glyburide did not result in any changes in either metformin pharmacokinetics or pharmacodynamics. Decreases in glyburide AUC and Cmaxwere observed, but were highly variable. The single-dose nature of this study and the lack of correlation between glyburide blood levels and pharmacodynamic effects, make the clinical significance of this interaction uncertain (see DOSAGE AND ADMINISTRATION: Concomitant Metformin and Oral Sulfonylurea Therapy in Adult Patients).

Furosemide—A single-dose, metformin-furosemide drug interaction study in healthy subjects demonstrated that pharmacokinetic parameters of both compounds were affected by co-administration. Furosemide increased the metformin plasma and blood Cmaxby 22% and blood AUC by 15%, without any significant change in metformin renal clearance. When administered with metformin, the Cmaxand AUC of furosemide were 31% and 12% smaller, respectively, than when administered alone, and the terminal half-life was decreased by 32%, without any significant change in furosemide renal clearance. No information is available about the interaction of metformin and furosemide when co-administered chronically.

Nifedipine—A single-dose, metformin-nifedipine drug interaction study in normal healthy volunteers demonstrated that co-administration of nifedipine increased plasma metformin Cmaxand AUC by 20% and 9%, respectively, and increased the amount excreted in the urine. Tmaxand half-life were unaffected. Nifedipine appears to enhance the absorption of metformin. Metformin had minimal effects on nifedipine.

Cationic drugs—Cationic drugs (e.g., amiloride, digoxin, morphine, procainamide, quinidine, quinine, ranitidine, triamterene, trimethoprim, or vancomycin) that are eliminated by renal tubular secretion theoretically have the potential for interaction with metformin by competing for common renal tubular transport systems. Such interaction between metformin and oral cimetidine has been observed in normal healthy volunteers in both single- and multiple-dose, metformin-cimetidine drug interaction studies, with a 60% increase in peak metformin plasma and whole blood concentrations and a 40% increase in plasma and whole blood metformin AUC. There was no change in elimination half-life in the single-dose study. Metformin had no effect on cimetidine pharmacokinetics. Although such interactions remain theoretical (except for cimetidine), careful patient monitoring and dose adjustment of metformin and/or the interfering drug is recommended in patients who are taking cationic medications that are excreted via the proximal renal tubular secretory system.

Other—Certain drugs tend to produce hyperglycemia and may lead to loss of glycemic control. These drugs include the thiazides and other diuretics, corticosteroids, phenothiazines, thyroid products, estrogens, oral contraceptives, phenytoin, nicotinic acid, sympathomimetics, calcium channel blocking drugs, and isoniazid. When such drugs are administered to a patient receiving metformin, the patient should be closely observed for loss of blood glucose control. When such drugs are withdrawn from a patient receiving metformin, the patient should be observed closely for hypoglycemia.

In healthy volunteers, the pharmacokinetics of metformin and propranolol, and metformin and ibuprofen were not affected when co-administered in single-dose interaction studies.

Metformin is negligibly bound to plasma proteins and is, therefore, less likely to interact with highly protein-bound drugs such as salicylates, sulfonamides, chloramphenicol, and probenecid, as compared to the sulfonylureas, which are extensively bound to serum proteins.

Carcinogenesis, Mutagenesis, Impairment of Fertility

Long-term carcinogenicity studies have been performed in rats (dosing duration of 104 weeks) and mice (dosing duration of 91 weeks) at doses up to and including 900 mg/kg/day and 1500 mg/kg/day, respectively. These doses are both approximately four times the maximum recommended human daily dose of 2000 mg based on body surface area comparisons. No evidence of carcinogenicity with metformin was found in either male or female mice. Similarly, there was no tumorigenic potential observed with metformin in male rats. There was, however, an increased incidence of benign stromal uterine polyps in female rats treated with 900 mg/kg/day.

There was no evidence of a mutagenic potential of metformin in the following in vitrotests: Ames test (S. typhimurium),gene mutation test (mouse lymphoma cells), or chromosomal aberrations test (human lymphocytes). Results in the in vivomouse micronucleus test were also negative.

Fertility of male or female rats was unaffected by metformin when administered at doses as high as 600 mg/kg/day, which is approximately three times the maximum recommended human daily dose based on body surface area comparisons.

Teratogenic Effects: Pregnancy Category B

Recent information strongly suggests that abnormal blood glucose levels during pregnancy are associated with a higher incidence of congenital abnormalities. Most experts recommend that insulin be used during pregnancy to maintain blood glucose levels as close to normal as possible. Because animal reproduction studies are not always predictive of human response, metformin should not be used during pregnancy unless clearly needed.

There are no adequate and well-controlled studies in pregnant women with metformin. Metformin was not teratogenic in rats and rabbits at doses up to 600 mg/kg/day. This represents an exposure of about two and six times the maximum recommended human daily dose of 2000 mg based on body surface area comparisons for rats and rabbits, respectively. Determination of fetal concentrations demonstrated a partial placental barrier to metformin.

Nursing Mothers

Studies in lactating rats show that metformin is excreted into milk and reaches levels comparable to those in plasma. Similar studies have not been conducted in nursing mothers. Because the potential for hypoglycemia in nursing infants may exist, a decision should be made whether to discontinue nursing or to discontinue the drug, taking into account the importance of the drug to the mother. If metformin is discontinued, and if diet alone is inadequate for controlling blood glucose, insulin therapy should be considered.

Pediatric Use

The safety and effectiveness of metformin hydrochloride tablets for the treatment of type 2 diabetes have been established in pediatric patients ages 10 to 16 years (studies have not been conducted in pediatric patients below the age of 10 years). Use of metformin hydrochloride tablets in this age group is supported by evidence from adequate and well-controlled studies of metformin hydrochloride tablets in adults with additional data from a controlled clinical study in pediatric patients ages 10 to 16 years with type 2 diabetes, which demonstrated a similar response in glycemic control to that seen in adults (see CLINICAL PHARMACOLOGY: Pediatric Clinical Studies). In this study, adverse effects were similar to those described in adults (see ADVERSE REACTIONS: Pediatric Patients). A maximum daily dose of 2000 mg is recommended (see DOSAGE AND ADMINISTRATION: Recommended Dosing Schedule: Pediatrics).

Geriatric Use

Controlled clinical studies of metformin did not include sufficient numbers of elderly patients to determine whether they respond differently from younger patients, although other reported clinical experience has not identified differences in responses between the elderly and younger patients. Metformin is known to be substantially excreted by the kidney and because the risk of serious adverse reactions to the drug is greater in patients with impaired renal function, metformin should only be used in patients with normal renal function (see CONTRAINDICATIONS, WARNINGS, and CLINICAL PHARMACOLOGY: Pharmacokinetics). Because aging is associated with reduced renal function, metformin should be used with caution as age increases. Care should be taken in dose selection and should be based on careful and regular monitoring of renal function. Generally, elderly patients should not be titrated to the maximum dose of metformin (see also WARNINGSand DOSAGE AND ADMINISTRATION).

ADVERSE REACTIONS

In a US double-blind clinical study of metformin hydrochloride tablets in patients with type 2 diabetes, a total of 141 patients received metformin hydrochloride tablets therapy (up to 2550 mg per day) and 145 patients received placebo. Adverse reactions reported in greater than 5% of the metformin hydrochloride tablets patients, and those were more common in metformin hydrochloride tablets- than placebo-treated patients, are listed in Table 7.

Table 7: Most Common Adverse Reactions (>5.0 Percent) in a Placebo-Controlled Clinical Study of Metformin Hydrochloride Tablets Monotherapy [Reactions those were more common in metformin - than placebo-treated patients.]
Adverse Reaction | Metformin HCl Monotherapy (n=141) | Placebo (n=145)
 | % of Patients
Diarrhea | 53.2 | 11.7
Nausea/Vomiting | 25.5 | 8.3
Flatulence | 12.1 | 5.5
Asthenia | 9.2 | 5.5
Indigestion | 7.1 | 4.1
Abdominal Discomfort | 6.4 | 4.8
Headache | 5.7 | 4.8

Diarrhea led to discontinuation of study medication in 6% of patients treated with metformin hydrochloride tablets. Additionally, the following adverse reactions were reported in ≥ 1.0 - ≤ 5.0% of metformin hydrochloride tablets patients and were more commonly reported with metformin hydrochloride tablets than placebo: abnormal stools, hypoglycemia, myalgia, lightheaded, dyspnea, nail disorder, rash, sweating increased, taste disorder, chest discomfort, chills, flu syndrome, flushing, palpitation.

Pediatric Patients

In clinical trials with metformin hydrochloride tablets in pediatric patients with type 2 diabetes, the profile of adverse reactions was similar to that observed in adults.

OVERDOSAGE

Overdose of metformin hydrochloride has occurred, including ingestion of amounts greater than 50 grams. Hypoglycemia was reported in approximately 10% of cases, but no causal association with metformin hydrochloride has been established. Lactic acidosis has been reported in approximately 32% of metformin overdose cases (see WARNINGS). Metformin is dialyzable with a clearance of up to 170 mL/min under good hemodynamic conditions. Therefore, hemodialysis may be useful for removal of accumulated drug from patients in whom metformin overdosage is suspected.

DOSAGE AND ADMINISTRATION

There is no fixed dosage regimen for the management of hyperglycemia in patients with type 2 diabetes with metformin or any other pharmacologic agent. Dosage of metformin must be individualized on the basis of both effectiveness and tolerance, while not exceeding the maximum recommended daily doses. The maximum recommended daily dose of metformin hydrochloride tablets is 2550 mg in adults and 2000 mg in pediatric patients (10 to 16 years of age).

Metformin hydrochloride tablets should be given in divided doses with meals. Metformin hydrochloride tablets should be started at a low dose, with gradual dose escalation, both to reduce gastrointestinal side effects and to permit identification of the minimum dose required for adequate glycemic control of the patient.

During treatment initiation and dose titration (see Recommended Dosing Schedule), fasting plasma glucose should be used to determine the therapeutic response to metformin hydrochloride tablets and identify the minimum effective dose for the patient. Thereafter, glycosylated hemoglobin should be measured at intervals of approximately three months. The therapeutic goal should be to decrease both fasting plasma glucose and glycosylated hemoglobin levels to normal or near normal by using the lowest effective dose of metformin hydrochloride tablets, either when used as monotherapy or in combination with sulfonylurea or insulin.

Monitoring of blood glucose and glycosylated hemoglobin will also permit detection of primary failure, i.e., inadequate lowering of blood glucose at the maximum recommended dose of medication, and secondary failure, i.e., loss of an adequate blood glucose lowering response after an initial period of effectiveness.

Short-term administration of metformin may be sufficient during periods of transient loss of control in patients usually well-controlled on diet alone.

Recommended Dosing Schedule

Adults

In general, clinically significant responses are not seen at doses below 1500 mg per day. However, a lower recommended starting dose and gradually increased dosage is advised to minimize gastrointestinal symptoms.

The usual starting dose of metformin hydrochloride tablets is 500 mg twice a day or 850 mg once a day, given with meals. Dosage increases should be made in increments of 500 mg weekly or 850 mg every two weeks, up to a total of 2000 mg per day, given in divided doses. Patients can also be titrated from 500 mg twice a day to 850 mg twice a day after two weeks. For those patients requiring additional glycemic control, metformin hydrochloride tablets may be given to a maximum daily dose of 2550 mg per day. Doses above 2000 mg may be better tolerated given three times a day with meals.

Pediatrics

The usual starting dose of metformin hydrochloride tablets is 500 mg twice a day, given with meals. Dosage increases should be made in increments of 500 mg weekly up to a maximum of 2000 mg per day, given in divided doses.

Transfer from Other Antidiabetic Therapy

When transferring patients from standard oral hypoglycemic agents other than chlorpropamide to metformin, no transition period generally is necessary. When transferring patients from chlorpropamide, care should be exercised during the first two weeks because of the prolonged retention of chlorpropamide in the body, leading to overlapping drug effects and possible hypoglycemia.

Concomitant Metformin and Oral Sulfonylurea Therapy in Adult Patients

If patients have not responded to four weeks of the maximum dose of metformin monotherapy, consideration should be given to gradual addition of an oral sulfonylurea while continuing metformin at the maximum dose, even if prior primary or secondary failure to a sulfonylurea has occurred. Clinical and pharmacokinetic drug-drug interaction data are currently available only for metformin plus glyburide (glibenclamide).

With concomitant metformin and sulfonylurea therapy, the desired control of blood glucose may be obtained by adjusting the dose of each drug. In a clinical trial of patients with type 2 diabetes and prior failure on glyburide, patients started on metformin hydrochloride tablets 500 mg and glyburide 20 mg were titrated to 1000/20 mg, 1500/20 mg, 2000/20 mg, or 2500/20 mg of metformin hydrochloride tablets and glyburide, respectively, to reach the goal of glycemic control as measured by FPG, HbA1c, and plasma glucose response (see CLINICAL PHARMACOLOGY: Clinical Studies). However, attempts should be made to identify the minimum effective dose of each drug to achieve this goal. With concomitant metformin and sulfonylurea therapy, the risk of hypoglycemia associated with sulfonylurea therapy continues and may be increased. Appropriate precautions should be taken. (See Package Insert of the respective sulfonylurea.)

If patients have not satisfactorily responded to one to three months of concomitant therapy with the maximum dose of metformin and the maximum dose of an oral sulfonylurea, consider therapeutic alternatives including switching to insulin with or without metformin.

Concomitant Metformin and Insulin Therapy in Adult Patients

The current insulin dose should be continued upon initiation of metformin therapy. Metformin therapy should be initiated at 500 mg once daily in patients on insulin therapy. For patients not responding adequately, the dose of metformin should be increased by 500 mg after approximately one week and by 500 mg every week thereafter until adequate glycemic control is achieved. The maximum recommended daily dose is 2500 mg for metformin hydrochloride tablets. It is recommended that the insulin dose be decreased by 10% to 25% when fasting plasma glucose concentrations decrease to less than 120 mg/dL in patients receiving concomitant insulin and metformin. Further adjustment should be individualized based on glucose-lowering response.

Specific Patient Populations

Metformin is not recommended for use in pregnancy. Metformin hydrochloride tablets is not recommended in patients below the age of 10 years.

The initial and maintenance dosing of metformin hydrochloride tablets should be conservative in patients with advanced age, due to the potential for decreased renal function in this population. Any dosage adjustment should be based on a careful assessment of renal function. Generally, elderly, debilitated, and malnourished patients should not be titrated to the maximum dose of metformin hydrochloride tablets.

Monitoring of renal function is necessary to aid in prevention of lactic acidosis, particularly in the elderly. (See WARNINGS.)

HOW SUPPLIED

Metformin Hydrochloride Tablets are available as follows:

Metformin Hydrochloride Tablets, USP 500 mg are blackberry flavored, white to off-white, round, biconvex, beveled edge film coated tablets, debossed with ‘SG’ on one side ‘105’ on other side.

500 mg:

1. Bottles of 60 NDC 60429-111-60
  Bottles of 90 NDC 60429-111-90
  Bottles of 100 NDC 60429-111-01
  Bottles of 120 NDC 60429-111-12
  Bottles of 180 NDC 60429-111-18
  Bottles of 270 NDC 60429-111-27
  Bottles of 360 NDC 60429-111-36
  Bottles of 450 NDC 60429-111-45
  Bottles of 1000 NDC 60429-111-10

Metformin Hydrochloride Tablets, USP 850 mg are blackberry flavored, white to off-white, round, biconvex, beveled edge film coated tablets, debossed with ‘SG’ on one side ‘106’ on other side.

850 mg:

1. Bottles of 60 NDC 60429-112-60
  Bottles of 90 NDC 60429-112-90
  Bottles of 100 NDC 60429-112-01
  Bottles of 180 NDC 60429-112-18
  Bottles of 270 NDC 60429-112-27
  Bottles of 500 NDC 60429-112-05

Metformin Hydrochloride Tablets, USP 1000 mg tablets are blackberry flavored, white to off-white, oval, biconvex, film coated tablets debossed on one side with S on the left side of bisect and G on the right side of bisect and other side 1 on the left side and 07 on the right side of the bisect.

1000 mg:

1. Bottles of 60 NDC 60429-113-60
  Bottles of 90 NDC 60429-113-90
  Bottles of 180 NDC 60429-113-18
  Bottles of 500 NDC 60429-113-05
  Bottles of 1000 NDC 60429-113-10

Storage

Store at 20°to 25° C (68°to 77° F); excursions permitted to 15° to 30° C (59° to 86° F). [See USP Controlled Room Temperature.]

Dispense in a tight, light-resistant container as defined in the USP.

Manufactured by:

Sciegen Pharmaceuticals, Inc
Hauppauge, NY 11788

Marketed/Packaged by:

GSMS, Inc.
Camarillo, CA 93012

Rev: 08/13

Rx Only

Patient Information

METFORMIN HYDROCHLORIDE TABLETS, USP

Read this information carefully before you start taking this medicine and each time you refill your prescription. There may be new information. This information does not take the place of your doctor’s advice. Ask your doctor or pharmacist if you do not understand some of this information or if you want to know more about this medicine.

What are metformin hydrochloride tablets?

Metformin hydrochloride tablets are used to treat type 2 diabetes. This is also known as non-insulin-dependent diabetes mellitus. People with type 2 diabetes are not able to make enough insulin or respond normally to the insulin their bodies make. When this happens, sugar (glucose) builds up in the blood. This can lead to serious medical problems including kidney damage, amputations, and blindness. Diabetes is also closely linked to heart disease. The main goal of treating diabetes is to lower your blood sugar to a normal level.

High blood sugar can be lowered by diet and exercise, by a number of medicines taken by mouth, and by insulin shots. Before you take metformin hydrochloride tablets, try to control your diabetes by exercise and weight loss. While you take your diabetes medicine, continue to exercise and follow the diet advised for your diabetes. No matter what your recommended diabetes management plan is, studies have shown that maintaining good blood sugar control can prevent or delay complications of diabetes, such as blindness.

Metformin hydrochloride tablets help control your blood sugar in a number of ways. These include helping your body respond better to the insulin it makes naturally, decreasing the amount of sugar your liver makes, and decreasing the amount of sugar your intestines absorb. Metformin hydrochloride tablets do not cause your body to make more insulin. Because of this, when taken alone, they rarely cause hypoglycemia (low blood sugar), and usually do not cause weight gain. However, when they are taken with a sulfonylurea or with insulin, hypoglycemia is more likely to occur, as is weight gain.

WARNING: A small number of people who have taken metformin hydrochloride tablets have developed a serious condition called lactic acidosis. Lactic acidosis is caused by a buildup of lactic acid in the blood. This happens more often in people with kidney problems. Most people with kidney problems should not take metformin hydrochloride tablets. (See "What are the side effects of metformin hydrochloride tablets?")

Who should not take metformin hydrochloride tablets?

Some conditions increase your chance of getting lactic acidosis, or cause other problems if you take either of these medicines. Most of the conditions listed below can increase your chance of getting lactic acidosis.

Do not take metformin hydrochloride tablets if you:

• have kidney problems

• have liver problems

• have heart failure that is treated with medicines, such as Lanoxin®(digoxin) or Lasix®(furosemide)

• drink a lot of alcohol. This means you binge drink for short periods or drink all the time

• are seriously dehydrated (have lost a lot of water from your body)

• are going to have an x-ray procedure with injection of dyes (contrast agents)

• are going to have surgery

• develop a serious condition, such as heart attack, severe infection, or a stroke

• are 80 years or older and you have NOT had your kidney function tested

Tell your doctor if you are pregnant or plan to become pregnant. Metformin hydrochloride tablets may not be right for you. Talk with your doctor about your choices. You should also discuss your choices with your doctor if you are nursing a child.

Can metformin hydrochloride tablets be used in children?

Metformin hydrochloride tablets has been shown to effectively lower glucose levels in children (ages 10 to 16 years) with type 2 diabetes. Metformin hydrochloride tablets has not been studied in children younger than 10 years old. Metformin hydrochloride tablets has not been studied in combination with other oral glucose-control medicines or insulin in children. If you have any questions about the use of metformin hydrochloride tablets in children, talk with your doctor or other healthcare provider.

How should I take metformin hydrochloride tablets?

Your doctor will tell you how much medicine to take and when to take it. You will probably start out with a low dose of the medicine.

Your doctor may slowly increase your dose until your blood sugar is better controlled. You should take metformin hydrochloride tablets with meals.

Your doctor may have you take other medicines along with metformin hydrochloride tablets to control your blood sugar. These medicines may include insulin shots. Taking metformin hydrochloride tablets with insulin may help you better control your blood sugar while reducing the insulin dose.

Continue your exercise and diet program and test your blood sugar regularly while taking metformin hydrochloride tablets. Your doctor will monitor your diabetes and may perform blood tests on you from time to time to make sure your kidneys and your liver are functioning normally. There is no evidence that metformin hydrochloride tablets causes harm to the liver or kidneys.

Tell your doctor if you:

• have an illness that causes severe vomiting, diarrhea or fever, or if you drink a much lower amount of liquid than normal. These conditions can lead to severe dehydration (loss of water in your body). You may need to stop taking metformin hydrochloride tablets for a short time.

• plan to have surgery or an x-ray procedure with injection of dye (contrast agent). You may need to stop taking metformin hydrochloride tablets for a short time.

• start to take other medicines or change how you take a medicine. Metformin hydrochloride tablets can affect how well other drugs work, and some drugs can affect how well metformin hydrochloride tablets work. Some medicines may cause high blood sugar.

What should I avoid while taking metformin hydrochloride tablets?

Do not drink a lot of alcoholic drinks while taking metformin hydrochloride tablets. This means you should not binge drink for short periods, and you should not drink a lot of alcohol on a regular basis. Alcohol can increase the chance of getting lactic acidosis.

What are the side effects of metformin hydrochloride tablets?

Lactic Acidosis.In rare cases, metformin hydrochloride tablets can cause a serious side effect called lactic acidosis. This is caused by a buildup of lactic acid in your blood. This buildup can cause serious damage. Lactic acidosis caused by metformin hydrochloride tablets is rare and has occurred mostly in people whose kidneys were not working normally. Lactic acidosis has been reported in about one in 33,000 patients taking metformin hydrochloride tablets over the course of a year. Although rare, if lactic acidosis does occur, it can be fatal in up to half the people who develop it.

It is also important for your liver to be working normally when you take metformin hydrochloride tablets. Your liver helps remove lactic acid from your blood.

Make sure you tell your doctor before you use metformin hydrochloride tablets if you have kidney or liver problems. You should also stop using metformin hydrochloride tablets and call your doctor right away if you have signs of lactic acidosis. Lactic acidosis is a medical emergency that must be treated in a hospital.

Signs of lactic acidosis are:

• feeling very weak, tired, or uncomfortable

• unusual muscle pain

• trouble breathing

• unusual or unexpected stomach discomfort

• feeling cold

• feeling dizzy or lightheaded

• suddenly developing a slow or irregular heartbeat

If your medical condition suddenly changes, stop taking metformin hydrochloride tablets and call your doctor right away. This may be a sign of lactic acidosis or another serious side effect.

Other Side Effects. Common side effects of metformin hydrochloride tablets include diarrhea, nausea, and upset stomach. These side effects generally go away after you take the medicine for a while. Taking your medicine with meals can help reduce these side effects. Tell your doctor if the side effects bother you a lot, last for more than a few weeks, come back after they’ve gone away, or start later in therapy. You may need a lower dose or need to stop taking the medicine for a short period or for good.

About 3 out of every 100 people who take metformin hydrochloride tablets have an unpleasant metallic taste when they start taking the medicine. It lasts for a short time.

Metformin hydrochloride tablets rarely cause hypoglycemia (low blood sugar) by themselves. However, hypoglycemia can happen if you do not eat enough, if you drink alcohol, or if you take other medicines to lower blood sugar.

General advice about prescription medicines

If you have questions or problems, talk with your doctor or other healthcare provider. You can ask your doctor or pharmacist for the information about metformin hydrochloride tablets that is written for healthcare professionals. Medicines are sometimes prescribed for purposes other than those listed in a patient information leaflet. Do not use metformin hydrochloride tablets for a condition for which it was not prescribed. Do not share your medicine with other people.

Other brands listed are the trademarks of their respective owners.

Dispense in a tight, light-resistant container as defined in the USP.

Manufactured by:
Sciegen Pharmaceuticals, Inc
Hauppauge, NY 11788

Marketed/Packaged by:
GSMS, Inc.
Camarillo, CA 93012

Rev: 05/14

Repackaging Information

Please reference the How Suppliedsection listed above for a description of individual tablets. This drug product has been received by Aphena Pharma - TN in a manufacturer or distributor packaged configuration and repackaged in full compliance with all applicable cGMP regulations. The package configurations available from Aphena are listed below:

Count | 500mg
30 | 43353-982-30
60 | 43353-982-53
90 | 43353-982-60
120 | 43353-982-70
180 | 43353-982-80
270 | 43353-982-92
360 | 43353-982-94
450 | 43353-982-96

Count | 850mg
30 | 43353-082-30
60 | 43353-082-53
90 | 43353-082-60
180 | 43353-082-80
270 | 43353-082-92
450 | 43353-082-96

Count | 1000mg
30 | 43353-987-30
45 | 43353-987-45
60 | 43353-987-53
90 | 43353-987-60
135 | 43353-987-73
180 | 43353-987-80
225 | 43353-987-86
450 | 43353-987-96
600 | 43353-987-31
1300 | 43353-987-43
2400 | 43353-987-87

Store between 20°-25°C (68°-77°F). See USP Controlled Room Temperature. Dispense in a tight light-resistant container as defined by USP. Keep this and all drugs out of the reach of children.

Repackaged by:
Cookeville, TN 38506
20240614AMH

PRINCIPAL DISPLAY PANEL - 500mg

NDC 43353-982 - Metformin HCl 500 mg Tablets - Rx Only

PRINCIPAL DISPLAY PANEL - 850mg

NDC 43353-082 - Metformin HCl 850 mg Tablets - Rx Only

PRINCIPAL DISPLAY PANEL - 1000mg

NDC 43353-987 - Metformin HCl 1000 mg Tablets - Rx Only